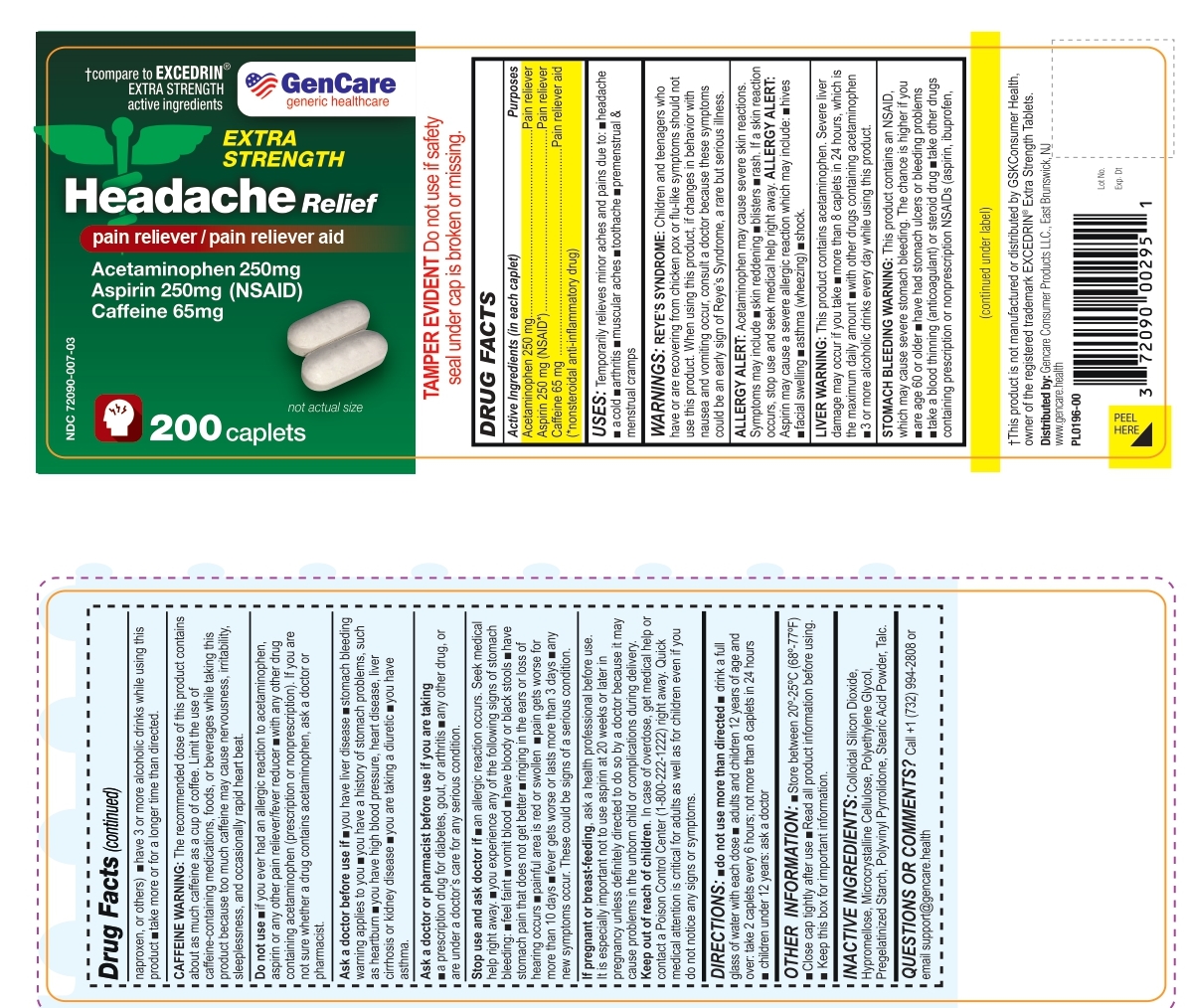 DRUG LABEL: GenCare Headache Relief
NDC: 72090-007 | Form: TABLET
Manufacturer: Pioneer Life Sciences, LLC
Category: otc | Type: HUMAN OTC DRUG LABEL
Date: 20251226

ACTIVE INGREDIENTS: CAFFEINE 65 mg/1 1; ACETAMINOPHEN 250 mg/1 1; ASPIRIN 250 mg/1 1
INACTIVE INGREDIENTS: SILICON DIOXIDE; HYPROMELLOSE, UNSPECIFIED; MICROCRYSTALLINE CELLULOSE; POLYETHYLENE GLYCOL, UNSPECIFIED; STARCH, CORN; POVIDONE K30; STEARIC ACID; TALC

Headache Relief

Active Ingredients (in each caplet)

Acetaminophen 250 mg

Aspirin 250 mg
Caffeine 65 mg

Purpose

Acetaminophen 250 mg............................................................Pain reliever
Aspirin 250 mg (NSAID*)..........................................................Pain reliever
Caffeine 65 mg ..................................................................Pain reliever aid
(*nonsteroidal anti-inflammatory drug)

Uses:

temporarily relieves minor aches and pains due to:

•headache
•a cold
•arthritis
•muscular aches
•toothache
•premenstrual & menstrual cramps

Warnings:

Reye’s syndrome:Children and teenagers who have or are recovering from chicken pox or flu-like symptoms should not use this product. When using this product, if changes in behavior with nausea and vomiting occur, consult a doctor because these symptoms could be an early sign of Reye’s syndrome, a rare but serious illness.

Allergy alert:Acetaminophen may cause severe skin reactions. Symptoms may include:

•skin reddening
•blisters
•rash

If a skin reaction occurs, stop use and seek medical help right away.

Allergy alert: Aspirin may cause a severe allergic reaction which may include:

•hives
•facial swelling
•asthma (wheezing)
•shock

Liver warning:This product contains acetaminophen. Severe liver damage may occur if you take

•more than 8 caplets in 24 hours, which is the maximum daily amount
•with other drugs containing acetaminophen
•3 or more alcoholic drinks every day while using this product

Stomach bleeding warning:This product contains an NSAID, which may cause severe stomach bleeding. The chance is higher if you

•are age 60 or older
•have had stomach ulcers or bleeding problems
•take a blood thinning (anticoagulant) or steroid drug
•take other drugs containing prescription or nonprescription NSAIDs (aspirin, ibuprofen, naproxen, or others)
•have 3 or more alcoholic drinks every day while using this product
•take more or for a longer time than directed

Caffeine warning:The recommended dose of this product contains about as much caffeine as a cup of coffee. Limit the use of caffeine-containing medications, foods, or beverages while taking this product because too much caffeine may cause nervousness, irritability, sleeplessness, and, occasionally, rapid heart beat.

Do not use

•if you have ever had an allergic reaction to acetaminophen, aspirin or any other pain reliever/fever reducer
•with any other drug containing acetaminophen (prescription or nonprescription). If you are not sure whether a drug contains acetaminophen, ask a doctor or pharmacist.

Ask Doctor:

Ask a doctor before use if

•you have liver disease
•stomach bleeding warning applies to you
•you have a history of stomach problems, such as heartburn
•you have high blood pressure, heart disease, liver cirrhosis, or kidney disease
•you are taking a diuretic
•you have asthma

ASK DOCTOR/PHARMACIST:

Ask a doctor or pharmacist before use if you are taking

•a prescription drug for diabetes, gout, or arthritis
•any other drug, or are under a doctor’s care for any serious condition

Stop use and ask doctor if

■an allergic reaction occurs. Seek medical help right away.

■you experience any of the following signs of stomach bleeding:

■feel faint

■vomit blood

■have bloody or black stools

■have
stomach pain that does not get better

■ringing in the ears or loss of
hearing occurs

■painful area is red or swollen

■pain gets worse for more than 10 days

■fever gets worse or lasts more than 3 days

■any new symptoms occur. These could be signs of a serious condition.

PREGNANCY

If pregnant or breast-feeding,ask a health professional before use. It is especially important not to use aspirin at 20 weeks or later in
pregnancy unless definitely directed to do so by a doctor because it may cause problems in the unborn child or complications during
delivery.

Keep out of reach of children.In case of overdose, get medical help or contact a Poison Control Center (1-800-222-1222) right
away. Quick medical attention is critical for adults as well as for children even if you do not notice any signs or symptoms.

DIRECTIONS

■ do not use more than directed

■ drink a full glass of water with each dose

■ adults and children 12 years of age and over: take 2 caplets every 6 hours; not more than 8 caplets in 24 hours
■ children under 12 years: ask a doctor

OTHER INFORMATION

■ Store between 20º-25ºC (68º-77ºF)
■ Close cap tightly after use

■ Read all product information before using.
■ Keep this box for important information.

INACTIVE INGREDIENTS

Colloidal Silicon Dioxide, Hypromellose, Microcrystalline Cellulose, Polyethylene Glycol, Pregelatinized Starch, Polyvinyl Pyrrolidone, Stearic Acid Powder, Talc.

QUESTIONS OR COMMENTS?

Call 1-732-994-2808 or email support@gencare.health